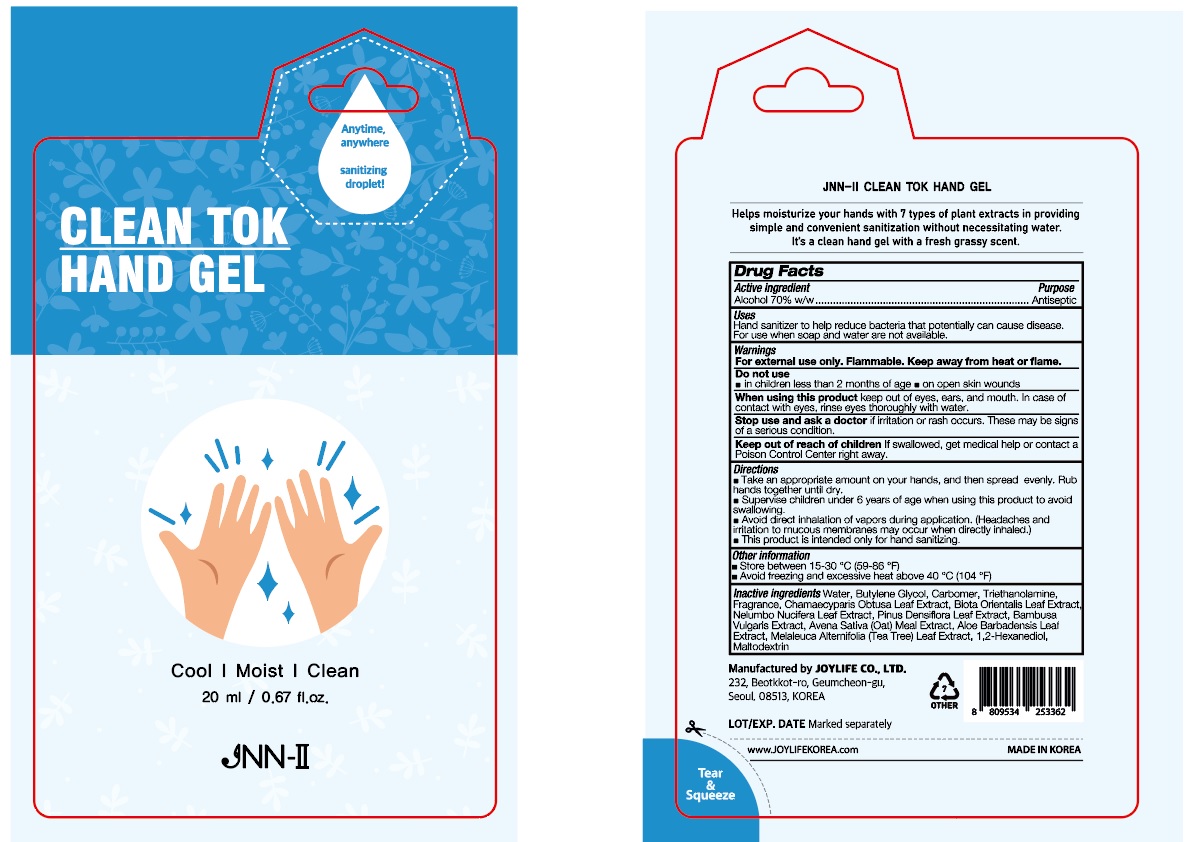 DRUG LABEL: JNN-II CLEAN TOK HAND Gel
NDC: 78424-020 | Form: GEL
Manufacturer: JOY LIFE Co., Ltd.
Category: otc | Type: HUMAN OTC DRUG LABEL
Date: 20200924

ACTIVE INGREDIENTS: ALCOHOL 14 mL/20 mL
INACTIVE INGREDIENTS: NELUMBO NUCIFERA LEAF; MALTODEXTRIN; BUTYLENE GLYCOL; CARBOMER HOMOPOLYMER, UNSPECIFIED TYPE; TROLAMINE; CHAMAECYPARIS OBTUSA LEAF; BAMBUSA VULGARIS TOP; ALOE VERA LEAF; MELALEUCA ALTERNIFOLIA LEAF; WATER; 1,2-HEXANEDIOL; PLATYCLADUS ORIENTALIS LEAF; PINUS DENSIFLORA LEAF; OATMEAL

JOY LIFE Co., Ltd. | JNN-II CLEAN TOK HAND GEL | 20 mL

PACKAGE LABEL

Active ingredient

Alcohol 70% w/w

Purpose

Antiseptic

Warnings

For external use only. Flammable. Keep away from heat or flame.

Do not use

■ in children less than 2 months of age ■ on open skin wounds

When using this product

keep out of eyes, ears, and mouth. In case of contact with eyes, rinse eyes thoroughly with water.

Stop use and ask a doctor

if irritation or rash occurs. These may be signs of a serious condition.

Keep out of reach of children

If swallowed, get medical help or contact a Poison Control Center right away.

Directions

■ Take an appropriate amount on your hands, and then spread evenly. Rub hands together until dry.

■ Supervise children under 6 years of age when using this product to avoid swallowing.

■ Avoid direct inhalation of vapors during application. (Headaches and irritation to mucous membranes may occur when directly inhaled.)

■ This product is intended only for hand sanitizing.

Other information

■ Store between 15-30 °C (59-86 °F)

■ Avoid freezing and excessive heat above 40 °C (104 °F)

Inactive ingredients

Water, Butylene Glycol, Carbomer, Triethanolamine, Fragrance, Chamaecyparis Obtusa Leaf Extract, Biota Orientalis Leaf Extract, Nelumbo Nucifera Leaf Extract, Pinus Densiflora Leaf Extract, Bambusa Vulgaris Extract, Avena Sativa (Oat) Meal Extract, Aloe Barbadensis Leaf Extract, Melaleuca Alternifolia (Tea Tree) Leaf Extract, 1,2-Hexanediol, Maltodextrin